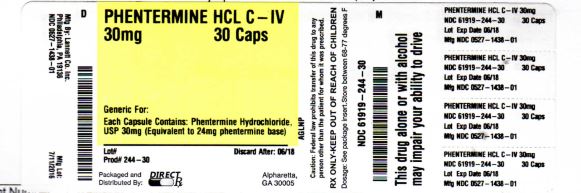 DRUG LABEL: PHENTERMINE HCL
NDC: 61919-244 | Form: CAPSULE
Manufacturer: DIRECT RX
Category: prescription | Type: HUMAN PRESCRIPTION DRUG LABEL
Date: 20160711
DEA Schedule: CIV

ACTIVE INGREDIENTS: PHENTERMINE HYDROCHLORIDE 30 mg/1 1
INACTIVE INGREDIENTS: POLYSORBATE 80; FD&C BLUE NO. 2; FD&C YELLOW NO. 6; D&C RED NO. 28; SHELLAC; ALCOHOL; BUTYL ALCOHOL; SUCROSE; STARCH, CORN; HYPROMELLOSES; POLYETHYLENE GLYCOLS; TITANIUM DIOXIDE; FD&C BLUE NO. 1; ALUMINUM OXIDE; GELATIN; FERROSOFERRIC OXIDE; PROPYLENE GLYCOL; METHYL ALCOHOL; FD&C RED NO. 40; D&C YELLOW NO. 10

PHENTERMINE HCL C-IV

INDICATIONS AND USAGE

Phentermine hydrochloride capsules are indicated as a short-term (a few weeks) adjunct in a regimen of weight reduction based on exercise, behavioral modification and caloric restriction in the management of exogenous obesity for patients with an initial body mass index ≥ 30 kg/m2, or ≥ 27 kg/m2 in the presence of other risk factors (e.g., controlled hypertension, diabetes, hyperlipidemia).

Below is a chart of body mass index (BMI) based on various heights and weights.

BMI is calculated by taking the patient’s weight, in kilograms (kg), divided by the patient’s height, in meters (m), squared. Metric conversions are as follows: pounds ÷ 2.2 = kg; inches x 0.0254 = meters.

BODY MASS INDEX (BMI), kg/m2

Height (feet, inches)
Weight
(pounds) 5'0" 5'3" 5'6" 5'9" 6'0" 6'3"
140 27 25 23 21 19 18
150 29 27 24 22 20 19
160 31 28 26 24 22 20
170 33 30 28 25 23 21
180 35 32 29 27 25 23
190 37 34 31 28 26 24
200 39 36 32 30 27 25
210 41 37 34 31 29 26
220 43 39 36 33 30 28
230 45 41 37 34 31 29
240 47 43 39 36 33 30
250 49 44 40 37 34 31
The limited usefulness of agents of this class, including phentermine, [see Clinical Pharmacology (12.1, 12.2)] should be measured against possible risk factors inherent in their use such as those described below.

DOSAGE AND ADMINISTRATION

Exogenous Obesity
Dosage should be individualized to obtain an adequate response with the lowest effective dose.

The usual adult dose is 15 mg to 30 mg as prescribed by the physician, at approximately 2 hours after breakfast for appetite control. Administration of one 30 mg capsule daily has been found to be adequate in depression of the appetite for 12 to 14 hours. Phentermine is not recommended for use in pediatric patients ≤ 16 years of age.

Late evening medication should be avoided because of the possibility of resulting insomnia.

DOSAGE FORMS AND STRENGTHS

Phentermine hydrochloride capsules USP, 15 mg (equivalent to 12 mg phentermine base): powder-filled capsules, gray/orange; imprinted logo LANNETT on the cap and 1742 on the body.
Phentermine hydrochloride capsules USP, 30 mg (equivalent to 24 mg phentermine base): powder-filled capsules, natural/blue; imprinted logo LANNETT on the cap and 1308 on the body.
Phentermine hydrochloride capsules USP, 30 mg (equivalent to 24 mg phentermine base): powder-filled capsules, yellow/yellow; imprinted logo LANNETT on the cap and 1310 on the body.
Phentermine hydrochloride capsules USP, 30 mg (equivalent to 24 mg phentermine base): powder-filled capsules, black/black; imprinted logo LANNETT on the cap and logo 0597 logo on the body.
Phentermine hydrochloride capsules USP, 30 mg (equivalent to 24 mg phentermine base): pellet-filled capsules, natural/blue; imprinted logo LANNETT on the cap and 1438 on the body.

CONTRAINDICATIONS

History of cardiovascular disease (e.g., coronary artery disease, stroke, arrhythmias, congestive heart failure, uncontrolled hypertension)
During or within 14 days following the administration of monoamine oxidase inhibitors
Hyperthyroidism
Glaucoma
Agitated states
History of drug abuse
Pregnancy [see Use in Specific Populations (8.1)]
Nursing [see Use in Specific Populations (8.3)]
Known hypersensitivity, or idiosyncrasy to the sympathomimetic amines

WARNINGS AND PRECAUTIONS

5.1 Coadministration with Other Drug Products for Weight Loss
Phentermine hydrochloride capsules are indicated only as short-term (a few weeks) monotherapy for the management of exogenous obesity. The safety and efficacy of combination therapy with phentermine and any other drug products for weight loss including prescribed drugs, over-the-counter preparations, and herbal products, or serotonergic agents such as selective serotonin reuptake inhibitors (e.g., fluoxetine, sertraline, fluvoxamine, paroxetine), have not been established. Therefore, coadministration of phentermine and these drug products is not recommended.

5.2 Primary Pulmonary Hypertension
Primary Pulmonary Hypertension (PPH) - a rare, frequently fatal disease of the lungs - has been reported to occur in patients receiving a combination of phentermine with fenfluramine or dexfenfluramine. The possibility of an association between PPH and the use of phentermine alone cannot be ruled out; there have been rare cases of PPH in patients who reportedly have taken phentermine alone. The initial symptom of PPH is usually dyspnea. Other initial symptoms may include angina pectoris, syncope or lower extremity edema. Patients should be advised to report immediately any deterioration in exercise tolerance. Treatment should be discontinued in patients who develop new, unexplained symptoms of dyspnea, angina pectoris, syncope or lower extremity edema, and patients should be evaluated for the possible presence of pulmonary hypertension.

5.3 Valvular Heart Disease
Serious regurgitant cardiac valvular disease, primarily affecting the mitral, aortic and/or tricuspid valves, has been reported in otherwise healthy persons who had taken a combination of phentermine with fenfluramine or dexfenfluramine for weight loss. The possible role of phentermine in the etiology of these valvulopathies has not been established and their course in individuals after the drugs are stopped is not known. The possibility of an association between valvular heart disease and the use of phentermine alone cannot be ruled out; there have been rare cases of valvular heart disease in patients who reportedly have taken phentermine alone.

5.4 Development of Tolerance, Discontinuation in Case of Tolerance
When tolerance to the anorectant effect develops, the recommended dose should not be exceeded in an attempt to increase the effect; rather, the drug should be discontinued.

5.5 Effect on the Ability to Engage in Potentially Hazardous Tasks
Phentermine may impair the ability of the patient to engage in potentially hazardous activities such as operating machinery or driving a motor vehicle; the patient should therefore be cautioned accordingly.

5.6 Risk of Abuse and Dependence
Phentermine is related chemically and pharmacologically to amphetamine (d- and dll-amphetamine) and other related stimulant drugs that have been extensively abused. The possibility of abuse of phentermine should be kept in mind when evaluating the desirability of including a drug as part of a weight reduction program. See Drug Abuse and Dependence (9) and Overdosage (10).

The least amount feasible should be prescribed or dispensed at one time in order to minimize the possibility of overdosage.

5.7 Usage with Alcohol
Concomitant use of alcohol with phentermine may result in an adverse drug reaction.

5.8 Use in Patients with Hypertension
Use caution in prescribing phentermine for patients with even mild hypertension (risk of increase in blood pressure).

5.9 Use in Patients on Insulin or Oral Hypoglycemic Medications for Diabetes Mellitus
A reduction in insulin or oral hypoglycemic medications in patients with diabetes mellitus may be required.

DRUG INTERACTIONS

7.1 Monoamine Oxidase Inhibitors
Use of phentermine is contraindicated during or within 14 days following the administration of monoamine oxidase inhibitors because of the risk of hypertensive crisis.

7.2 Alcohol
Concomitant use of alcohol with phentermine may result in an adverse drug reaction.

7.3 Insulin and Oral Hypoglycemic Medications
Requirements may be altered [see Warnings and Precautions (5.9)].

7.4 Adrenergic Neuron Blocking Drugs
Phentermine may decrease the hypotensive effect of adrenergic neuron blocking drugs.

DRUG ABUSE AND DEPENDENCE

9.1 Controlled Substance
Phentermine is a Schedule IV controlled substance.

9.2 Abuse
Phentermine is related chemically and pharmacologically to the amphetamines. Amphetamines and other stimulant drugs have been extensively abused and the possibility of abuse of phentermine should be kept in mind when evaluating the desirability of including a drug as part of a weight reduction program.

9.3 Dependence
Abuse of amphetamines and related drugs may be associated with intense psychological dependence and severe social dysfunction. There are reports of patients who have increased the dosage of these drugs to many times than recommended. Abrupt cessation following prolonged high dosage administration results in extreme fatigue and mental depression; changes are also noted on the sleep EEG. Manifestations of chronic intoxication with anorectic drugs include severe dermatoses, marked insomnia, irritability, hyperactivity and personality changes. A severe manifestation of chronic intoxication is psychosis, often clinically indistinguishable from schizophrenia.

OVERDOSAGE

The least amount feasible should be prescribed or dispensed at one time in order to minimize the possibility of overdosage.

10.1 Acute Overdosage
Manifestations of acute overdosage include restlessness, tremor, hyperreflexia, rapid respiration, confusion, assaultiveness, hallucinations, and panic states. Fatigue and depression usually follow the central stimulation. Cardiovascular effects include arrhythmia, hypertension or hypotension, and circulatory collapse. Gastrointestinal symptoms include nausea, vomiting, diarrhea and abdominal cramps. Overdosage of pharmacologically similar compounds has resulted in fatal poisoning usually terminates in convulsions and coma.

Management of acute phentermine hydrochloride intoxication is largely symptomatic and includes lavage and sedation with a barbiturate. Experience with hemodialysis or peritoneal dialysis is inadequate to permit recommendations in this regard. Acidification of the urine increases phentermine excretion. Intravenous phentolamine (Regitine®, CIBA) has been suggested on pharmacologic grounds for possible acute, severe hypertension, if this complicates overdosage.

10.2 Chronic Intoxication
Manifestations of chronic intoxication with anorectic drugs include severe dermatoses, marked insomnia, irritability, hyperactivity and personality changes. The most severe manifestation of chronic intoxications is psychosis, often clinically indistinguishable from schizophrenia. See Drug Abuse and Dependence (9.3).

NONCLINICAL TOXICOLOGY

13.1 Carcinogenesis, Mutagenesis, Impairment of Fertility
Studies have not been performed with phentermine to determine the potential for carcinogenesis, mutagenesis or impairment of fertility.

HOW SUPPLIED

Store at 20° to 25°C (68° to 77°F) [See USP Controlled Room Temperature].

Dispense in a tight container as defined in the USP, with a child-resistant closure (as required).

Keep out of the reach of children.